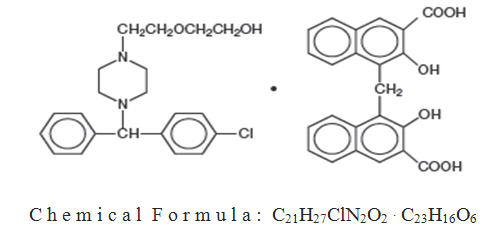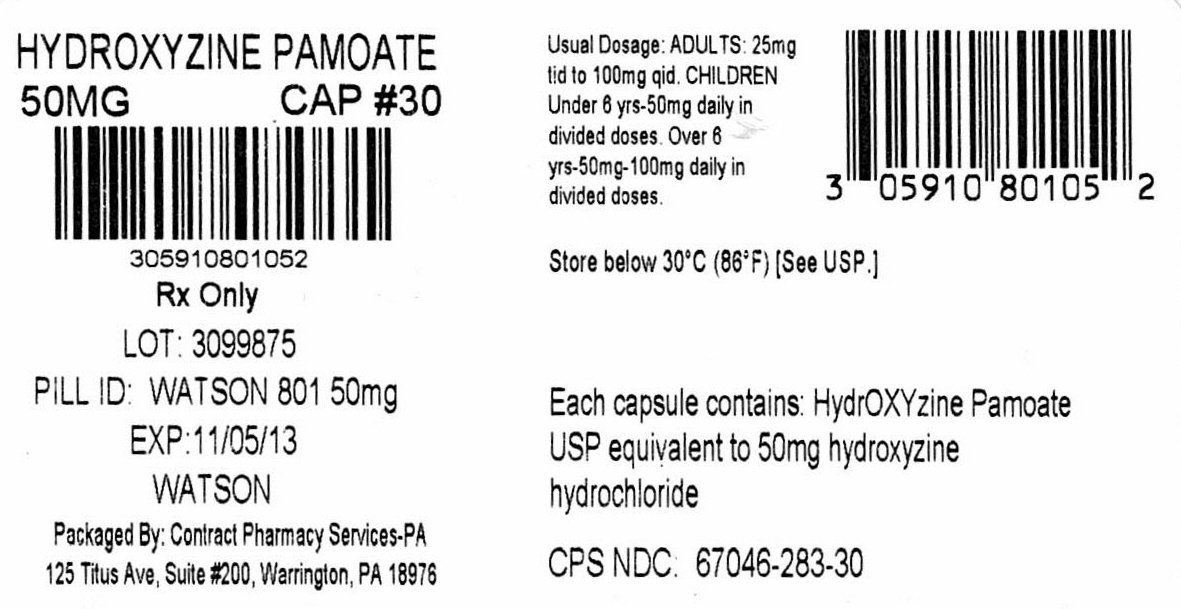 DRUG LABEL: Hydroxyzine Pamoate
NDC: 67046-283 | Form: CAPSULE
Manufacturer: Contract Pharmacy Services-PA
Category: prescription | Type: HUMAN PRESCRIPTION DRUG LABEL
Date: 20171004

ACTIVE INGREDIENTS: HYDROXYZINE PAMOATE 50 mg/1 1
INACTIVE INGREDIENTS: SILICON DIOXIDE; D&C YELLOW NO. 10; FD&C BLUE NO. 1; GELATIN; MAGNESIUM STEARATE; STARCH, CORN; SODIUM LAURYL SULFATE; TITANIUM DIOXIDE; FERROSOFERRIC OXIDE

283 Hydroxyzine Pamoate 50 mg
HydrOXYzine Pamoate Capsules USP
Rx only

DESCRIPTION

Hydroxyzine pamoate is a light yellow, practically odorless powder practically insoluble in water and methanol and freely soluble in dimethylformamide. It is chemically designated as 1-(p-chlorobenzhydryl) 4-[2-(2-hydroxyethoxy) ethyl] diethylenediamine salt of 1,1’-methylene bis (2hydroxy-3-naphthalene carboxylic acid) and can be structurally represented as follows:

Molecular Weight: 763.29

Each capsule, for oral administration, contains hydroxyzine pamoate equivalent to 25 mg or 50 mg of hydroxyzine hydrochloride. In addition, each capsule contains the following inactive ingredients: colloidal silicon dioxide, D&C yellow #10, FD&C blue #1, gelatin, magnesium stearate, pregelatinized starch, sodium lauryl sulfate, and titanium dioxide. The imprinting ink on the capsules contains synthetic black iron oxide.

CLINICAL PHARMACOLOGY

Hydroxyzine pamoate is unrelated chemically to the phenothiazines, reserpine, meprobamate, or the benzodiazepines. Hydroxyzine pamoate is not a cortical depressant, but its action may be due to a suppression of activity in certain key regions of the subcortical area of the central nervous system. Primary skeletal muscle relaxation has been demonstrated experimentally. Bronchodilator activity, and antihistaminic and analgesic effects have been demonstrated experimentally and confirmed clinically. An antiemetic effect, both by the apomorphine test and the veriloid test, has been demonstrated. Pharmacological and clinical studies indicate that hydroxyzine in therapeutic dosage does not increase gastric secretion or acidity and in most cases has mild antisecretory activity. Hydroxyzine is rapidly absorbed from the gastrointestinal tract and hydroxyzine pamoate's clinical effects are usually noted within 15 to 30 minutes after oral administration.

INDICATIONS

For symptomatic relief of anxiety and tension associated with psychoneurosis and as an adjunct in organic disease states in which anxiety is manifested.

Useful in the management of pruritus due to allergic conditions such as chronic urticaria and atopic and contact dermatoses, and in histamine-mediated pruritus.

As a sedative when used as premedication and following general anesthesia, Hydroxyzine may potentiate meperidine (Demerol®) and barbiturates , so their use in pre-anesthetic adjunctive therapy should be modified on an individual basis. Atropine and other belladonna alkaloids are not affected by the drug. Hydroxyzine is not known to interfere with the action of digitalis in any way and it may be used concurrently with this agent.

The effectiveness of hydroxyzine as an antianxiety agent for long-term use, that is, more than 4 months, has not been assessed by systematic clinical studies. The physician should reassess periodically the usefulness of the drug for the individual patient.

CONTRAINDICATIONS

Hydroxyzine, when administered to the pregnant mouse, rat, and rabbit, induced fetal abnormalities in the rat and mouse at doses substantially above the human therapeutic range. Clinical data in human beings are inadequate to establish safety in early pregnancy. Until such data are available, hydroxyzine is contraindicated in early pregnancy.

Hydroxyzine pamoate is contraindicated for patients who have shown a previous hypersensitivity to any component of this medication.

WARNINGS

Nursing Mothers

It is not known whether this drug is excreted in human milk. Since many drugs are so excreted, hydroxyzine should not be given to nursing mothers.

PRECAUTIONS

THE POTENTIATING ACTION OF HYDROXYZINE MUST BE CONSIDERED WHEN THE DRUG IS USED IN CONJUNCTION WITH CENTRAL NERVOUS SYSTEM DEPRESSANTS SUCH AS NARCOTICS, NON-NARCOTIC ANALGESICS AND BARBITURATES. Therefore, when central nervous system depressants are administered concomitantly with hydroxyzine, their dosage should be reduced. Since drowsiness may occur with use of the drug, patients should be warned of this possibility and cautioned against driving a car or operating dangerous machinery while taking hydroxyzine pamoate. Patients should be advised against the simultaneous use of other CNS depressant drugs, and cautioned that the effect of alcohol may be increased.

Geriatric Use

A determination has not been made whether controlled clinical studies of hydroxyzine pamoate included sufficient numbers of subjects aged 65 and over to define a difference in response from younger subjects. Other reported clinical experience has not identified differences in responses between the elderly and younger patients. In general, dose selection for an elderly patient should be cautious, usually starting at the low end of the dosing range, reflecting the greater frequency of decreased hepatic, renal or cardiac function and of concomitant disease or other drug therapy.

The extent of renal excretion of hydroxyzine pamoate has not been determined. Because elderly patients are more likely to have decreased renal function, care should be taken in dose selections. Sedating drugs may cause confusion and over sedation in the elderly; elderly patients generally should be started on low doses of hydroxyzine pamoate and observed closely.

ADVERSE REACTIONS

Side effects reported with the administration of hydroxyzine pamoate are usually mild and transitory in nature.

Anticholinergic: Dry mouth.

Central Nervous System: Drowsiness is usually transitory and may disappear in a few days of continued therapy or upon reduction of the dose. Involuntary motor activity, including rare instances of tremor and convulsions, has been reported, usually with doses considerably higher than those recommended. Clinically significant respiratory depression has not been reported at recommended doses.

In post-marketing experience, the following additional undesirable effects have been reported: Body as a Whole: allergic reaction, Nervous System: headache, Psychiatric: hallucination, Skin and Appendages: pruritus, rash, urticaria.

OVERDOSAGE

The most common manifestation of overdosage of hydroxyzine pamoate is hypersedation. Other reported signs and symptoms were convulsions, stupor, nausea and vomiting. As in the management of overdosage with any drug, it should be borne in mind that multiple agents may have been taken.

If vomiting has not occurred spontaneously, it should be induced. Immediate gastric lavage is also recommended. General supportive care, including frequent monitoring of the vital signs and close observation of the patient, is indicated. Hypotension, though unlikely, may be controlled with intravenous fluids and vasopressors (do not use epinephrine as hydroxyzine counteracts its pressor action.) Caffeine and Sodium Benzoate Injection, USP, may be used to counteract central nervous system depressant effects. There is no specific antidote. It is doubtful that hemodialysis would be of any value in the treatment of overdosage with hydroxyzine. However, if other agents such as barbiturates have been ingested concomitantly, hemodialysis may be indicated. There is no practical method to quantitate hydroxyzine in body fluids or tissue after its ingestion or administration.

DOSAGE

For symptomatic relief of anxiety and tension associated with psychoneurosis and as an adjunct in organic disease states in which anxiety is manifested: in adults, 50 mg to 100 mg q.i.d.; children under 6 years, 50 mg daily in divided doses; and over 6 years, 50 mg to 100 mg daily in divided doses.

For use in the management of pruritus due to allergic conditions such as chronic urticaria and atopic and contact dermatoses, and in histamine-mediated pruritus: in adults, 25 mg t.i.d. or q.i.d.; children under 6 years, 50 mg daily in divided doses; and over 6 years, 50 mg to 100 mg daily in divided doses.

As a sedative when used as a premedication and following general anesthesia: 50 mg to 100 mg in adults, and 0.6 mg/kg in children. When treatment is initiated by the intramuscular route of administration, subsequent doses may be administered orally.

As with all medications, the dosage should be adjusted according to the patient's response to therapy.

HOW SUPPLIED

Hydroxyzine pamoate capsules USP (hydroxyzine pamoate equivalent to hydroxyzine hydrochloride) are supplied as follows:

50 mg capsules: Dark green opaque cap/white opaque body filled with yellow powder. Imprinted in black ink WATSON over 801 on the cap and 50 mg on the body, in the following:

NDC 67046-283-07 blisterpacks of 7

NDC 67046-283-14 blisterpacks of 14

NDC 67046-283-15 blisterpacks of 15

NDC 67046-283-20 blisterpacks of 20

NDC 67046-283-21 blisterpacks of 21

NDC 67046-283-28 blisterpacks of 28

NDC 67046-283-30 blisterpacks of 30

NDC 67046-283-60 blisterpacks of 60

Store below 30°C (86°F) [See USP].

Dispense in a tight, light resistant container as defined in USP/NF.

BIBLIOGRAPHY

Available on request.

Manufactured by:
Patheon Pharmaceuticals Inc.
Cincinnati, OH 45237 USA

Manufactured for:
Watson Pharma, Inc.
Parsippany, NJ 07054 USA

Revised: 05/2012

70025267

Repackaged by:
Contract Pharmacy Services-PA
125 Titus Ave Suite 200
Warrington, PA 18976 USA

Rev: Original—2017.10.04—NJW

PRINCIPAL DISPLAY PANEL

NDC 67046-283-30
HydrOXYzine
Pamoate
Capsules USP
50 mg*
Tartrazine Dye-Free
Watson 30 Capsules Rx only

*Each capsule contains:
HydrOXYzine Pamoate USP equivalent to 50 mg
Hydroxyzine Hydrochloride
Usual dosage: ADULTS: 25 mg tid to 100 mg qid.
CHILDREN: Under 6 years - 50 mg daily in divided doses.
Over 6 years - 50 mg to 100 mg daily in divided doses.
Dispense in a tight, light-resistant container as defined
in USP/NF.
Store below 30ºC (86ºF). [See USP.]
Keep out of reach of children.
Manufactured By:
Patheon Pharmaceuticals Inc.
Cincinnati, OH 45237 USA
DIstributed By: Watson Pharma, Inc.